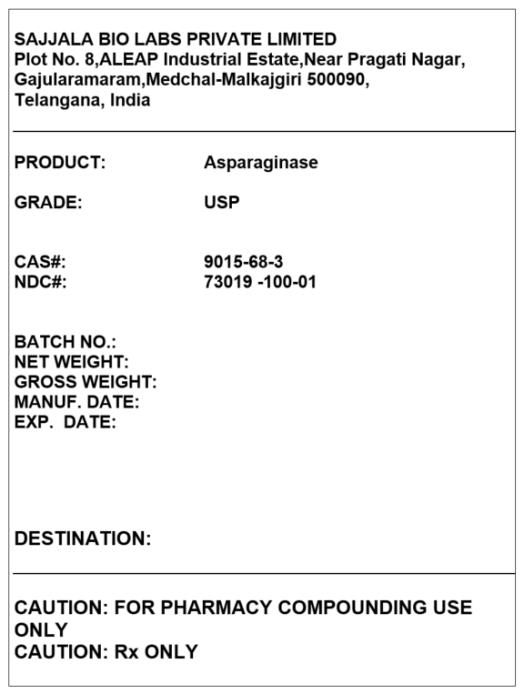 DRUG LABEL: Asparaginase
NDC: 73019-0100 | Form: POWDER
Manufacturer: SAJJALA BIO LABS PRIVATE LIMITED
Category: other | Type: BULK INGREDIENT
Date: 20200317

ACTIVE INGREDIENTS: ASPARAGINASE 1 g/1 g

Asparaginase

PRINCIPAL DISPLAY PANEL – BULK PRODUCT

SAJJALA BIO LABS PRIVATE LIMITED
Plot No. 8,ALEAP Industrial Estate,Near Pragati Nagar,

Gajularamaram,Medchal-Malkajgiri 500090, Telangana, India

PRODUCT: Asparaginase
GRADE: USP
CAS#: 9015-68-3
NDC#: 73019 -100-01

CAUTION: FOR PHARMACY COMPOUNDING USE ONLY
CAUTION: Rx ONLY